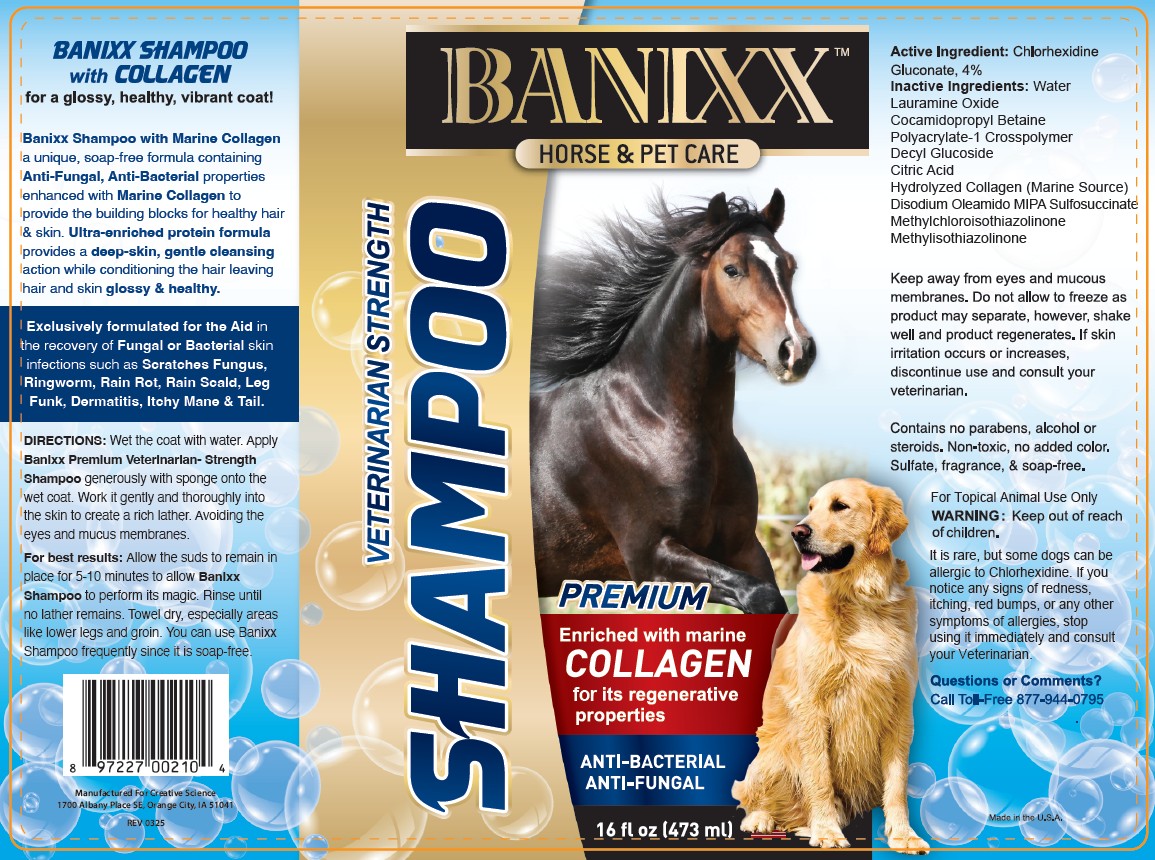 DRUG LABEL: BANIXX with COLLAGEN
NDC: 86099-116 | Form: SHAMPOO
Manufacturer: Creative Science
Category: animal | Type: OTC ANIMAL DRUG LABEL
Date: 20251118

ACTIVE INGREDIENTS: CHLORHEXIDINE GLUCONATE 40 mg/1 mL
INACTIVE INGREDIENTS: WATER; LAURAMINE OXIDE; COCAMIDOPROPYL BETAINE; DECYL GLUCOSIDE; CITRIC ACID MONOHYDRATE; MARINE COLLAGEN, SOLUBLE; DISODIUM OLEAMIDO MIPA-SULFOSUCCINATE; METHYLCHLOROISOTHIAZOLINONE; METHYLISOTHIAZOLINONE

BANIXX SHAMPOO with COLLAGEN VETERINARIAN STRENGTH

Active Ingredient: Chlorhexidine Gluconate, 4%

PURPOSE

ANTI-FUNGAL
ANTI-BACTERIAL

INDICATIONS AND USAGE

Banixx Shampoo with Marine Collagen a unique, soap-free formula containing Anti-Fungal, Anti-Bacterial properties enhanced with Marine Collagen to provide the building blocks for healthy hair & skin. Ultra-enriched protein formula provides a deep-skin, gentle cleansing action while conditioning the hair leaving hair and skin glossy & healthy.

Exclusively formulated for the Aid in the recovery of Fungal or Bacterial skin infections such as Scratches Fungus, Ringworm, Rain Rot, Rain Scald, Leg Funk, Dermatitis, Itchy Mane & Tail.

WARNINGS

Keep away from eyes and mucous membranes. Do not allow to freeze as product may separate, however, shake well and product regenerates. If skin irritation occurs or increases, discontinue use and consult your veterinarian.

For Topical Animal Use Only

It is rare, but some dogs can be allergic to Chlorhexidine. If you notice any signs of redness, itching, red bumps, or any other symptoms of allergies, stop using it immediately and consult your Veterinarian.

WARNING: Keep out of reach of children.

DOSAGE AND ADMINISTRATION

DIRECTIONS: Wet the coat with water. Apply Banixx Premium Veterinarian-Strength Shampoo generously with sponge onto the wet coat. Work it gently and thoroughly into the skin to create a rich lather. Avoiding the eyes and mucus membranes.

For best results: Allow the suds to remain in place for 5-10 minutes to allow Banixx Shampoo to perform its magic. Rinse until no lather remains. Towel dry, especially areas like lower legs and groin. You can use Banixx Shampoo frequently since it is soap-free.

QUESTIONS

Contains no parabens, alcohol or steroids. Non-toxic, no added color. Sulfate, fragrance & soap-free.

Questions or Comments?

Call Toll-Free 877-944-0795

Inactive Ingredients :
Water
Lauramine Oxide
Cocamidopropyl Betaine
Polyacrylate-1 Crosspolymer
Decyl Glucoside
Citric Acid
Hydrolyzed Collagen (Marine Source)
Disodium Oleamido MIPA Sulfosuccinate
Methylchloroisothiazolinone
Methylisothiazolinone

UPC 897227002104

Manufactured for Creative Science 1700 Albany Place SE Orange City, IA 51041

REV 0325

PACKAGE LABEL

Banixx

HORSE & PET CARE

Veterinarian Strength Shampoo

PREMIUM

Enriched with marine COLLAGEN for its regenerative properties

Anti-Bacterial

Anti-Fungal

16 fl oz (473 ml)